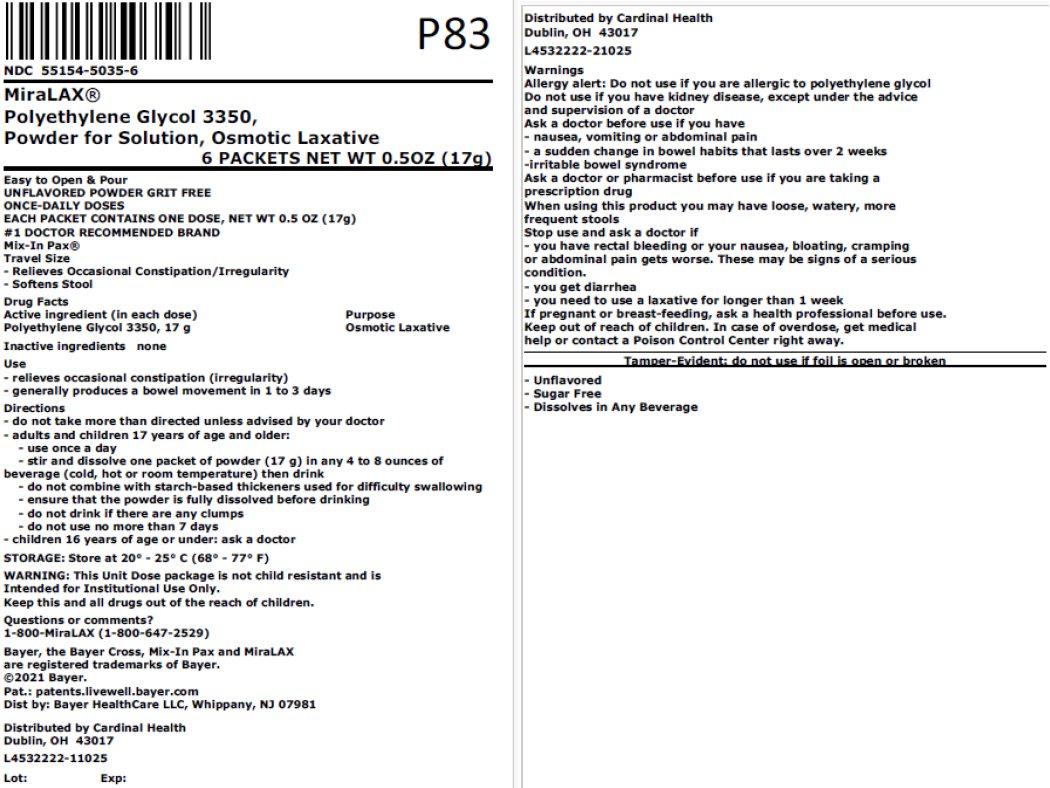 DRUG LABEL: MiraLAX
NDC: 55154-5035 | Form: POWDER, FOR SOLUTION
Manufacturer: Cardinal Health 107, LLC
Category: otc | Type: HUMAN OTC DRUG LABEL
Date: 20251107

ACTIVE INGREDIENTS: POLYETHYLENE GLYCOL 3350 17 g/17 g

MiraLAX ®

Drug Facts

Active ingredient (in each dose) (Bottle Only)

Polyethylene Glycol 3350, 17 g (cap filled to line)

Purpose

Osmotic Laxative

Active ingredient (in each dose) (Packet Only)

Polyethylene Glycol 3350, 17 g

Purpose

Osmotic Laxative

Use

- relieves occasional constipation (irregularity)
- generally produces a bowel movement in 1 to 3 days

Warnings

Allergy alert

Do not use if you are allergic to polyethylene glycol

Do not use if you have kidney disease, except under the advice and supervision of a doctor

Ask a doctor before use if you have

- nausea, vomiting or abdominal pain
- a sudden change in bowel habits that lasts over 2 weeks
- irritable bowel syndrome

Ask a doctor of pharmacist before use if you are taking a prescription drug

When using this product you may have loose, watery, more frequent stools

Stop use and ask a doctor if

- you have rectal bleeding or you nausea, bloating or cramping or abdominal pain gets worse. These may be signs of a serious condition.
- you get diarrhea
- you need to use a laxative for longer than 1 week

PREGNANCY OR BREAST FEEDING

If pregnant or breast-feeding, ask a health professional before use.

KEEP OUT OF REACH OF CHILDREN

Keep out of the reach of children. In case of overdose, get medical help or contact a Poison Control Center right away.

Directions (Bottle Only)

- do not take more than directed unless advised by your doctor
- the bottle top is a measuring cap marked to contain 17 grams of powder when filled to the indicated line (white section in cap)
- adults and children 17 years of age and older:
  - use once a day
  - fill to top of white section in cap which is marked to indicate the correct dose (17 g)
  - stir and dissolve in any 4 to 8 ounces of beverage (cold, hot or room temperature) then drink
  - do not combine with starch-based thickeners used for difficulty swallowing
  - ensure that the powder is fully dissolved before drinking
  - do not drink if there are any clumps
  - do not use no more than 7 days
- children 16 years of age or under: ask a doctor

Directions (Packet Only)

- do not take more than directed unless advised by your doctor
- adults and children 17 years of age and older:
  - use once a day
  - stir and dissolve one packet of powder (17 g) in any 4 to 8 ounces of beverage (cold, hot or room temperature) then drink
  - do not combine with starch-based thickeners used for difficulty swallowing
  - ensure that the powder is fully dissolved before drinking
  - do not drink if there are any clumps
  - do not use more than 7 days
- children 16 years of age or under: ask a doctor

Other information

- store at 20°-25°C (68°-77°F)
- tamper-evident: do not use if foil seal under cap, printed with "SEALED for YOUR PROTECTION" is missing, open or broken

Inactive ingredients

none

Questions or comments?

1-800-MiraLAX (1-800-647-2529)

.

Overbagged with 6 x 17g packets per bag, NDC 55154-5035-6

WARNING: This Unit Dose package is not child resistant and is Intended for Institutional Use Only. Keep this and all drugs out of the reach of children.

Distributed By:

Cardinal Health

Dublin, OH 43017

L4532222-11025 / L4532222-21025

Principal Display Panel

NDC 55154-5035-6

MiraLAX®

Polyethylene Glycol 3350,

Powder for Solution, Osmotic Laxative

6 PACKETS NET WT 0.5OZ (17g)